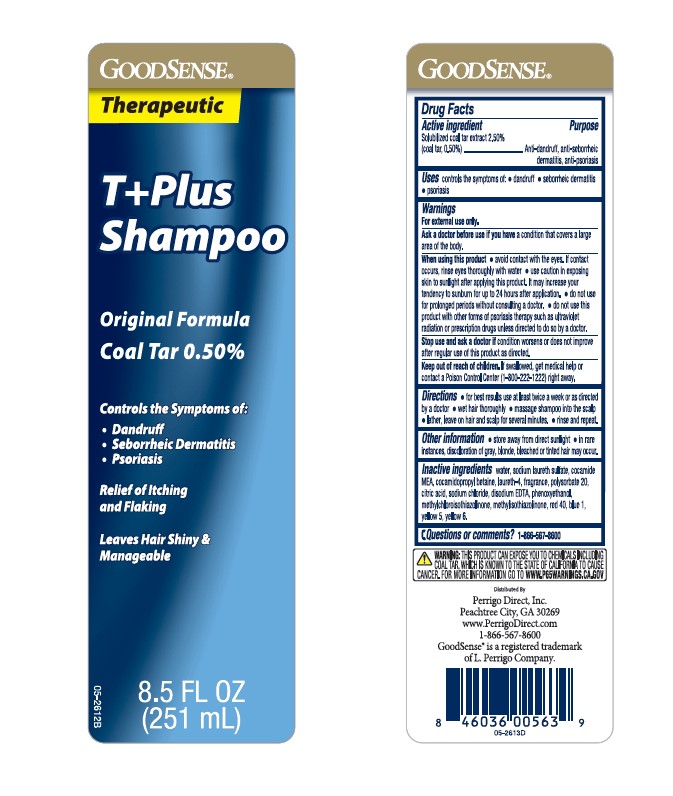 DRUG LABEL: therapeutic tar anti-dandruff
NDC: 50804-887 | Form: SHAMPOO
Manufacturer: GOODSENSE
Category: otc | Type: HUMAN OTC DRUG LABEL
Date: 20251208

ACTIVE INGREDIENTS: COAL TAR 5 mg/1 mL
INACTIVE INGREDIENTS: Water; SODIUM LAURYL SULFATE; COCO MONOETHANOLAMIDE; Cocamidopropyl Betaine; Laureth-4; Polysorbate 20; CITRIC ACID MONOHYDRATE; Sodium Chloride; EDETATE DISODIUM; Phenoxyethanol; Methylchloroisothiazolinone; Methylisothiazolinone; FD&C RED NO. 40; FD&C BLUE NO. 1; FD&C YELLOW NO. 5; FD&C YELLOW NO. 6

amazon basics therapeutic tar gel anti-dandruff shampoo
Anti-dandruff, anti-seborrheic dermatitis, anti-psoriasis

Drug Facts

Active ingredient

Solubilized Coal Tar Extract 2.50% (Coal Tar, 0.50%)

Purpose

Anti-dandruff, anti-seborrheic dermatitis, anti-psoriasis

Use

controls the symptom of:

- dandruff
- seborrheic dermatitis
- psoriasis

Warnings

For External use only.

Ask a doctor before using this product if condition covers a large area of the body.

When using this product

- avoid contact with the eyes. If contact occurs, rinse eyes thoroughly with water
- use caution in exposing skin to sunlight after applying this product. It may increase your tendency to sunburn for up to 24 hours after application.
- do not use for prolonged periods without consulting a doctor.
- do not use this product with other forms of psoriasis therapy such as ultraviolet radiation or prescription drugs unless directed to do so by a doctor.

Stop use and ask a doctor if condition worsens or does not improve after regular use of this product as directed.

Keep out of reach of children. If swallowed, get medical help or contact a Poison Control Center (1-800-222-1222) right away.

Directions

- for best results use at least twice a week or as directed by a doctor
- wet hair thoroughly
- massage shampoo into the scalp
- lather, leave on hair and scalp for several minutes.
- rinse and repeat

Other information

- store away from direct sunlight
- in rare instances, discoloration of gray, blonde, bleached or tinted hair may occur

Inactive ingredients

water, sodium laureth sulfate, cocamide MEA, cocamidopropyl betaine, laureth-4, fragrance, polysorbate 20, citric acid, sodium chloride, disodium EDTA, phenoxyethanol, methylchloroisothiazolinone, methylisothiazolinone, red 40, blue 1, yellow 5, yellow 6.

Questions or comments?

1-866-567-8600

Distributed by:
Perrigo Direct, Inc.
Peachtree City, GA 30269
www.PerrigoDirect.com
1-866-567-8600
GoodSense is a registered trademark
of L Perrigo Company .

PRINCIPAL DISPLAY PANEL - 251 mL Bottle Label

GOODSENSE

Therapeutic

T+Plus

Shampoo

Original Formula

Coal Tar 0.50%

Controls Symptoms of:

Dandruff

Seborrheic Dermatitis

Psoriasis

Relief of Itching

and Flaking

Leave Hair Shiny &

Manageable

0.5%
COAL
TAR

8.5 FL OZ (251 mL)

GoodSense Original